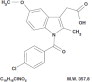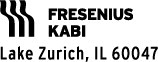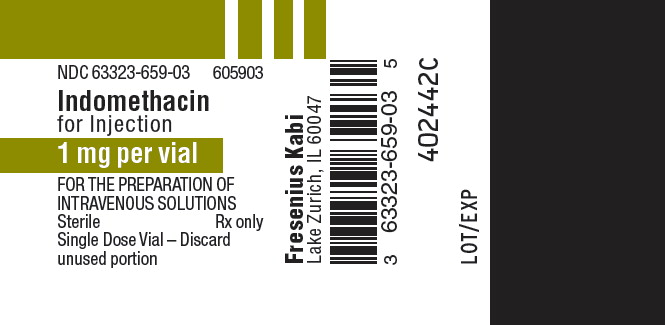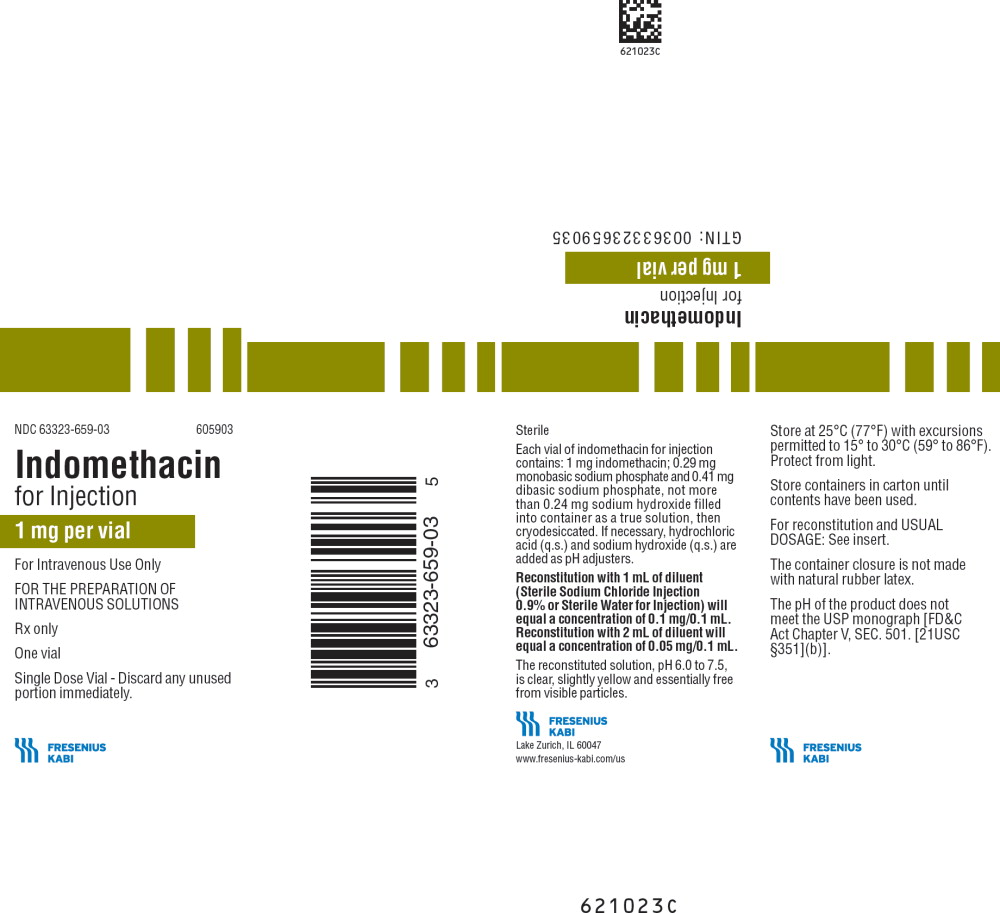 DRUG LABEL: Indomethacin
NDC: 63323-659 | Form: INJECTION, POWDER, LYOPHILIZED, FOR SOLUTION
Manufacturer: Fresenius Kabi USA, LLC
Category: prescription | Type: HUMAN PRESCRIPTION DRUG LABEL
Date: 20260119

ACTIVE INGREDIENTS: INDOMETHACIN 1 mg/1 mL
INACTIVE INGREDIENTS: SODIUM PHOSPHATE, MONOBASIC, UNSPECIFIED FORM 0.29 mg/1 mL; SODIUM PHOSPHATE, DIBASIC, UNSPECIFIED FORM 0.41 mg/1 mL; SODIUM HYDROXIDE; HYDROCHLORIC ACID

HIGHLIGHTS OF PRESCRIBING INFORMATION

These highlights do not include all the information needed to use Indomethacin for Injection safely and effectively. See full prescribing information for Indomethacin for Injection.
Indomethacin for Injection Initial U.S. Approval: 1965

1 INDICATIONS AND USAGE

Indomethacin for Injection is a cardiovascular drug indicated:

- To close a hemodynamically significant patent ductus arteriosus in premature infants weighing between 500 and 1,750 g. (1)

2 DOSAGE AND ADMINISTRATION

- Dosage is dependent on the age of the infant at time of therapy. A course of therapy requires intravenous doses of Indomethacin for Injection given at 12 to 24 hour intervals.

AGE at 1st dose | DOSAGE (mg/kg)
Less than 48 hours | 1st 0.2 | 2nd 0.1 | 3rd 0.1
2 to 7 days | 0.2 | 0.2 | 0.2
Over 7 days | 0.2 | 0.25 | 0.25

- If anuria or marked oliguria (urinary output <0.6 mL/kg/hr) is evident at the scheduled time of the second or third dose of Indomethacin for Injection, do not give additional doses until laboratory studies indicate that renal function has returned to normal
- If the ductus arteriosus closes or is significantly reduced in size after an interval of 48 hours or more from completion of the first course of Indomethacin for Injection, no further doses are necessary
- If the neonate remains unresponsive to therapy with Indomethacin for Injection after 2 courses, surgery may be necessary for closure of the ductus arteriosus. (2.1)

3 DOSAGE FORMS AND STRENGTHS

- Single dose vials of 1 mg indomethacin as a sterile, lyophilized powder or plug for reconstitution. (3)

4 CONTRAINDICATIONS

Indomethacin for Injection is contraindicated in neonates:

- With proven or suspected infection that is untreated
- Who are bleeding, especially those with active intracranial hemorrhage or gastrointestinal bleeding
- With thrombocytopenia or coagulation defects
- Suspected of having necrotizing enterocolitis
- With significant impairment of renal function
- With congenital heart disease in whom patency of the ductus arteriosus is necessary for satisfactory pulmonary or systemic blood flow. (4)

5 WARNINGS AND PRECAUTIONS

- Indomethacin may mask the usual signs of infection. (5.1)
- Monitor for signs of hepatic reactions. Indomethacin for Injection may need to be discontinued. (5.2)
- Indomethacin for Injection may inhibit platelet aggregation. (5.3)
- Gastrointestinal Effects: Monitor neonates for blood in stool. (5.4)
- Central Nervous System Effects: Monitor neonates for intraventricular hemorrhage. (5.5)
- Renal Effects: Monitor renal function and serum electrolytes. (5.6)

6 ADVERSE REACTIONS

Most common adverse reactions are bleeding problems, higher incidence of transient oliguria and elevations of serum creatinine. (6.1)

To report SUSPECTED ADVERSE REACTIONS, contact Fresenius Kabi USA, LLC at 1-800-551-7176 or FDA at 1-800-FDA-1088 or www.fda.gov/medwatch.

7 DRUG INTERACTIONS

- When used concomitantly with digoxin, monitor neonates for the development of digoxin toxicity. (7.1)
- Monitor prothrombin time when indomethacin is added to anticoagulants. (7.2)

FULL PRESCRIBING INFORMATION

1 INDICATIONS AND USAGE

Indomethacin for Injection is indicated to close a hemodynamically significant patent ductus arteriosus in premature infants weighing between 500 and 1,750 g when 48 hours usual medical management (e.g., fluid restriction, diuretics, digitalis, respiratory support, etc.) is ineffective. Clear-cut clinical evidence of a hemodynamically significant patent ductus arteriosus should be present, such as respiratory distress, a continuous murmur, a hyperactive precordium, cardiomegaly, or pulmonary plethora on chest x-ray.

2 DOSAGE AND ADMINISTRATION

For intravenous administration only.

Dosage recommendations for closure of the ductus arteriosus depend on the age of the infant at the time of therapy. A course of therapy is defined as three intravenous doses of Indomethacin for Injection given at 12 to 24 hour intervals, with careful attention to urinary output. If anuria or marked oliguria (urinary output <0.6 mL/kg/hr) is evident at the scheduled time of the second or third dose of Indomethacin for Injection, do not give additional doses until laboratory studies indicate that renal function has returned to normal [see Warnings and Precautions (5.7)].

Dosage according to age is as follows:

AGE at 1st dose | DOSAGE (mg/kg)
Less than 48 hours | 1st 0.2 | 2nd 0.1 | 3rd 0.1
2 to 7 days | 0.2 | 0.2 | 0.2
Over 7 days | 0.2 | 0.25 | 0.25

If the ductus arteriosus closes or is significantly reduced in size after an interval of 48 hours or more from completion of the first course of Indomethacin for Injection, no further doses are necessary. If the ductus arteriosus re-opens, a second course of 1 to 3 doses may be given, each dose separated by a 12 to 24 hour interval as described above.

If the neonate remains unresponsive to therapy with Indomethacin for Injection after 2 courses, surgery may be necessary for closure of the ductus arteriosus.

2.1 Directions for Use

Parenteral drug products should be inspected visually for particulate matter and discoloration prior to administration whenever solution and container permit.

The reconstituted solution, pH 6.0 to 7.5, is clear, slightly yellow and essentially free from visible particles.

Prepare the solution with 1 to 2 mL of preservative-free Sterile Sodium Chloride Injection, 0.9 percent or preservative-free Sterile Water for Injection. Benzyl alcohol as a preservative has been associated with toxicity in neonates. Therefore, do not use diluents that contain preservatives. If 1 mL of diluent is used, the concentration of indomethacin in the solution will equal approximately 0.1 mg/0.1 mL; if 2 mL of diluent are used, the concentration of the solution will equal approximately 0.05 mg/0.1 mL. Discard any unused portion of the solution as it does not contain a preservative. Prepare a fresh solution just prior to each administration. Once reconstituted, the indomethacin solution may be injected intravenously. While the optimal rate of injection has not been established, published literature suggests an infusion rate over 20 to 30 minutes.

Further dilution with intravenous infusion solutions is not recommended.

3 DOSAGE FORMS AND STRENGTHS

Indomethacin for Injection is supplied in single dose vials containing 1 mg of indomethacin as a sterile lyophilized powder or plug for reconstitution.

4 CONTRAINDICATIONS

Indomethacin for Injection is contraindicated in neonates:

- With proven or suspected infection that is untreated
- Who are bleeding, especially those with active intracranial hemorrhage or gastrointestinal bleeding
- With thrombocytopenia or coagulation defects
- With or who are suspected of having necrotizing enterocolitis
- With significant impairment of renal function
- With congenital heart disease in whom patency of the ductus arteriosus is necessary for satisfactory pulmonary or systemic blood flow (e.g., pulmonary atresia, severe tetralogy of Fallot, severe coarctation of the aorta).

5 WARNINGS AND PRECAUTIONS

5.1 Infection

Indomethacin may mask the usual signs and symptoms of infection. Therefore, the physician must be continually on the alert for this and should use the drug with extra care in the presence of existing controlled infection.

5.2 Hepatic Reactions

Severe hepatic reactions have been reported in adults treated chronically with oral indomethacin for arthritic disorders. [For further information, see package insert for oral indomethacin]. If clinical signs and symptoms consistent with liver disease develop in the neonate, or if systemic manifestations occur, discontinue Indomethacin for Injection.

5.3 Platelet Aggregation

Indomethacin for Injection may inhibit platelet aggregation. In one small study, platelet aggregation was grossly abnormal after indomethacin therapy (given orally to premature infants to close the ductus arteriosus). Platelet aggregation returned to normal by the tenth day. Observe premature infants for signs of bleeding.

5.4 Gastrointestinal Effects

In the collaborative study, major gastrointestinal bleeding was no more common in neonates receiving indomethacin than in neonates on placebo. However, minor gastrointestinal bleeding (i.e., chemical detection of blood in the stool) was more commonly noted in neonates treated with indomethacin.

Severe gastrointestinal effects have been reported in adults with various arthritic disorders treated chronically with oral indomethacin. [For further information, see package insert for oral indomethacin].

5.5 Central Nervous System Effects

Prematurity per se is associated with an increased incidence of spontaneous intraventricular hemorrhage. Because indomethacin may inhibit platelet aggregation, the potential for intraventricular bleeding may be increased. However, in the large multicenter study of Indomethacin for Injection, the incidence of intraventricular hemorrhage in neonates treated with Indomethacin for Injection was not significantly higher than in the control neonates.

5.6 Renal Effects

Indomethacin for Injection may cause significant reduction in urine output (50 percent or more) with concomitant elevations of blood urea nitrogen and creatinine, and reductions in glomerular filtration rate and creatinine clearance. These effects in most neonates are transient, disappearing with cessation of therapy with Indomethacin for Injection. However, because adequate renal function can depend upon renal prostaglandin synthesis, Indomethacin for Injection may precipitate renal insufficiency, including acute renal failure, especially in neonates with other conditions that may adversely affect renal function (e.g., extracellular volume depletion from any cause, congestive heart failure, sepsis, concomitant use of any nephrotoxic drug, hepatic dysfunction). When significant suppression of urine volume occurs after a dose of Indomethacin for Injection, do not give additional doses until urine output returns to normal levels.

Indomethacin for Injection in pre-term infants may suppress water excretion to a greater extent than sodium excretion. When this occurs, a significant reduction in serum sodium values (i.e., hyponatremia) may result. Monitor renal function and serum electrolyte levels during therapy with Indomethacin for Injection [see Dosage and Administration (2)].

5.7 Administration

Administer Indomethacin for Injection carefully to avoid extravascular injection or leakage as the solution may be irritating to tissue.

6 ADVERSE REACTIONS

6.1 Clinical Trials Experience

In a double-blind, placebo-controlled trial of 405 premature infants weighing less than or equal to 1,750 g with evidence of large ductal shunting, in those neonates treated with indomethacin (n=206), there was a statistically significantly greater incidence of bleeding problems, including gross or microscopic bleeding into the gastrointestinal tract, oozing from the skin after needle stick, pulmonary hemorrhage, and disseminated intravascular coagulopathy. There was no statistically significant difference between treatment groups in intracranial hemorrhage.

The neonates treated with Indomethacin for Injection had a significantly higher incidence of transient oliguria and elevations of serum creatinine (greater than or equal to 1.8 mg/dL) than did the neonates treated with placebo.

The incidences of retrolental fibroplasia (grades III and IV) and pneumothorax in neonates treated with Indomethacin for Injection were no greater than in placebo controls and were statistically significantly lower than in surgically-treated neonates.

The following additional adverse reactions in neonates have been reported from the collaborative study, anecdotal case reports, from other studies using rectal, oral, or intravenous indomethacin for treatment of patent ductus arteriosus or in marketed use. The rates are calculated from a database that contains experience of 849 indomethacin-treated neonates reported in the medical literature, regardless of the route of administration. One year follow-up is available on 175 neonates and shows no long-term sequelae that could be attributed to indomethacin. In controlled clinical studies, only electrolyte imbalance and renal dysfunction (of the reactions listed below) occurred statistically significantly more frequently after Indomethacin for Injection than after placebo. Reactions marked with a single asterisk (*) occurred in 3 to 9 percent of indomethacin-treated neonates; those marked with a double asterisk (**) occurred in 3 to 9 percent of both indomethacin- and placebo-treated neonates. Unmarked reactions occurred in less than 3 percent of neonates.

Renal: renal failure, renal dysfunction in 41 percent of neonates, including one or more of the following: reduced urinary output; reduced urine sodium, chloride, or potassium, urine osmolality, free water clearance, or glomerular filtration rate; elevated serum creatinine or BUN; uremia.

Cardiovascular: intracranial bleeding**, pulmonary hypertension.

Gastrointestinal: gastrointestinal bleeding*, vomiting, abdominal distention, transient ileus, gastric perforation, localized perforation(s) of the small and/or large intestine, necrotizing enterocolitis.

Metabolic: hyponatremia*, elevated serum potassium*, reduction in blood sugar, including hypoglycemia, increased weight gain (fluid retention).

Coagulation: decreased platelet aggregation [see Warnings and Precautions (5.3)].

The following adverse reactions have also been reported in neonates treated with indomethacin, however, a causal relationship to therapy with Indomethacin for Injection has not been established:

Cardiovascular: bradycardia.

Respiratory: apnea, exacerbation of pre-existing pulmonary infection.

Metabolic: acidosis/alkalosis.

Hematologic: disseminated intravascular coagulation, thrombocytopenia.

Ophthalmic: retrolental fibroplasia.**

Dermatologic: drug reaction with eosinophilia and systemic symptoms (DRESS)

A variety of additional adverse experiences have been reported in adults treated with oral indomethacin for moderate to severe rheumatoid arthritis, osteoarthritis, ankylosing spondylitis, acute painful shoulder and acute gouty arthritis (see package insert for oral indomethacin for additional information concerning adverse reactions and other cautionary statements). Their relevance to the pre-term infant receiving indomethacin for patent ductus arteriosus is unknown, however, the possibility exists that these experiences may be associated with the use of Indomethacin for Injection in pre-term infants.

7 DRUG INTERACTIONS

As renal function may be reduced by Indomethacin for Injection, consider reducing the dosage of those medications that rely on adequate renal function for their elimination.

7.1 Digoxin

Because the half-life of digoxin (given frequently to pre-term infants with patent ductus arteriosus and associated cardiac failure) may be prolonged when given concomitantly with indomethacin, observe neonates receiving concomitant digoxin closely; frequent ECGs and serum digoxin levels may be required to prevent or detect digoxin toxicity early.

7.2 Anticoagulants

Indomethacin usually does not influence the hypoprothrombinemia produced by anticoagulants. When indomethacin is added to anticoagulants, monitor prothrombin time closely. In post-marketing experience, bleeding has been reported in patients on concomitant treatment with anticoagulants and Indomethacin for Injection.

7.3 Furosemide

Therapy with indomethacin may blunt the natriuretic effect of furosemide. This response has been attributed to inhibition of prostaglandin synthesis by non-steroidal anti-inflammatory drugs. In a study of 19 premature infants with patent ductus arteriosus treated with either Indomethacin for Injection alone or a combination of Indomethacin for Injection and furosemide, results showed that neonates receiving both Indomethacin for Injection and furosemide had significantly higher urinary output, higher levels of sodium and chloride excretion, and higher glomerular filtration rates than did those receiving Indomethacin for Injection alone. In this study, therapy with furosemide helped to maintain renal function in the premature infant when Indomethacin for Injection was added.

7.4 Aminoglycosides

In one study of premature infants treated with Indomethacin for Injection and also receiving either gentamicin or amikacin, both peak and trough levels of these aminoglycosides were significantly elevated.

7.5 Drugs that Act on the Renin-Angiotensin System

In some patients with compromised renal function, the co-administration of an NSAID and an ACE inhibitor or angiotensin II antagonist may result in further deterioration of renal function, including possible acute renal failure, which is usually reversible.

11 DESCRIPTION

Sterile Indomethacin for Injection for intravenous administration is lyophilized indomethacin for injection. Each vial of indomethacin for injection contains 1 mg indomethacin; 0.29 mg monobasic sodium phosphate, 0.41 mg dibasic sodium phosphate and not more than 0.24 mg of sodium hydroxide (used for converting indomethacin base to the sodium salt) as a white to yellow lyophilized powder or plug. Variations in the size of the lyophilized plug and the intensity of color have no relationship to the quality or amount of indomethacin present in the vial. If necessary, hydrochloric acid (q.s.) and sodium hydroxide (q.s.) are added as pH adjusters. The reconstituted solution, pH 6.0 to 7.5, is clear, slightly yellow and essentially free from visible particles. The pH of the product does not meet the USP monograph [FD&C Act Chapter V, SEC. 501. [21USC §351](b)].

Indomethacin is designated chemically as 1-(4-chlorobenzoyl)-5-methoxy-2-methyl-1H-indole-3-acetic acid. The structural formula is:

12 CLINICAL PHARMACOLOGY

12.1 Mechanism of Action

Although the exact mechanism of action through which indomethacin causes closure of a patent ductus arteriosus is not known, it is believed to be through inhibition of prostaglandin synthesis.

12.2 Pharmacodynamics

Indomethacin has been shown to be a potent inhibitor of prostaglandin synthesis, both in vitro and in vivo. In human newborns with certain congenital heart malformations, PGE 1 dilates the ductus arteriosus. In fetal and newborn lambs, E type prostaglandins have also been shown to maintain the patency of the ductus, and as in human newborns, indomethacin causes its constriction.

Studies in healthy young animals and in premature infants with patent ductus arteriosus indicated that, after the first dose of intravenous indomethacin, there was a transient reduction in cerebral blood flow velocity and cerebral blood flow. Similar decreases in mesenteric blood flow and velocity have been observed. The clinical significance of these effects has not been established.

In double-blind, placebo-controlled studies of Indomethacin for Injection in 460 small pre-term infants, weighing 1,750 g or less, the neonates treated with placebo had a ductus closure rate after 48 hours of 25 to 30 percent, whereas those treated with Indomethacin for Injection had a 75 to 80 percent closure rate. In one of these studies, a multicenter study, involving 405 pre-term infants, later reopening of the ductus arteriosus occurred in 26 percent of neonates treated with Indomethacin for Injection however, 70 percent of these closed subsequently without the need for surgery or additional indomethacin.

12.3 Pharmacokinetics

The disposition of indomethacin following intravenous administration (0.2 mg/kg) in pre-term neonates with patent ductus arteriosus has not been extensively evaluated. Even though the plasma half-life of indomethacin was variable among premature infants, it was shown to vary inversely with postnatal age and weight. In one study, of 28 neonates who could be evaluated, the plasma half-life in those less than 7 days old averaged 20 hours (range: 3 to 60 hours, n=18). In neonates older than 7 days, the mean plasma half-life of indomethacin was 12 hours (range: 4 to 38 hours, n=10). Grouping the neonates by weight, mean plasma half-life in those weighing less than 1,000 g was 21 hours (range: 9 to 60 hours, n=10); in those neonates weighing more than 1,000 g, the mean plasma half-life was 15 hours (range: 3 to 52 hours, n=18).

Following intravenous administration in adults, indomethacin is eliminated via renal excretion, metabolism, and biliary excretion. Indomethacin undergoes appreciable enterohepatic circulation. The mean plasma half-life of indomethacin is 4.5 hours. In the absence of enterohepatic circulation, it is 90 minutes. Indomethacin has been found to cross the blood-brain barrier and the placenta.

In adults, about 99 percent of indomethacin is bound to protein in plasma over the expected range of therapeutic plasma concentrations. The percent bound in neonates has not been studied. In controlled trials in premature infants, however, no evidence of bilirubin displacement has been observed as evidenced by increased incidence of bilirubin encephalopathy (kernicterus).

13 NONCLINICAL TOXICOLOGY

In rats and mice, oral indomethacin 4 mg/kg/day given during the last three days of gestation caused a decrease in maternal weight gain and some maternal and fetal deaths. An increased incidence of neuronal necrosis in the diencephalon in the live-born fetuses was observed. At 2 mg/kg/day, no increase in neuronal necrosis was observed as compared to the control groups. Administration of 0.5 or 4 mg/kg/day during the first three days of life did not cause an increase in neuronal necrosis at either dose level.

Pregnant rats, given 2 mg/kg/day and 4 mg/kg/day during the last trimester of gestation, delivered offspring whose pulmonary blood vessels were both reduced in number and excessively muscularized. These findings are similar to those observed in the syndrome of persistent pulmonary hypertension of the neonate.

16 HOW SUPPLIED/STORAGE AND HANDLING

16.1 How Supplied

Sterile Indomethacin for Injection is a lyophilized white to yellow powder or plug supplied as single dose vials containing indomethacin for injection, equivalent to 1 mg indomethacin.

Product No. | NDC No.
605903 | 63323-659-03 | 1 mg per vial, Packaged individually.

The container closure is not made with natural rubber latex.

16.2 Storage

Store at 25°C (77°F) with excursions permitted to 15° to 30°C (59° to 86°F). Protect from light. Store container in carton until contents have been used.

www.fresenius-kabi.com/us

451150C

PACKAGE LABEL

PACKAGE LABEL - PRINCIPAL DISPLAY - Indomethacin for Injection 1 mg Vial Label

NDC 63323-659-03 605903

Indomethacin
for Injection

1 mg per vial

FOR THE PREPARATION OF INTRAVENOUS SOLUTIONS

Sterile Rx only

Single Dose Vial -
Discard unused portion

PACKAGE LABEL

PACKAGE LABEL - PRINCIPAL DISPLAY - Indomethacin for Injection 1 mg Carton Panel

NDC 63323-659-03 605903

Indomethacin
for Injection

1 mg per vial

For Intravenous Use Only

FOR THE PREPARATION OF INTRAVENOUS SOLUTIONS

Rx only

One vial

Single Dose Vial - Discard any unused portion immediately.